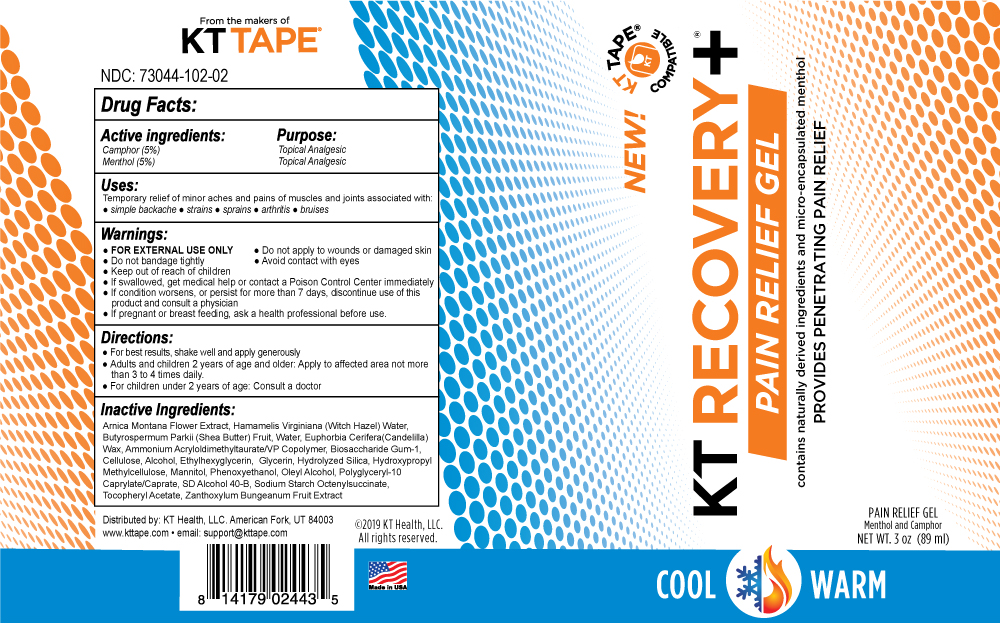 DRUG LABEL: KT Recovery Plus  Pain Relief Gel
NDC: 73044-102 | Form: GEL
Manufacturer: KT Health LLC
Category: otc | Type: HUMAN OTC DRUG LABEL
Date: 20241118

ACTIVE INGREDIENTS: MENTHOL 50 mg/1 mL; CAMPHOR (NATURAL) 50 mg/1 mL
INACTIVE INGREDIENTS: ZANTHOXYLUM BUNGEANUM FRUIT; OLEYL ALCOHOL; .ALPHA.-TOCOPHEROL ACETATE; ETHYLHEXYLGLYCERIN; MANNITOL; EUPHORBIA ANTISYPHILITICA WHOLE; MICROCRYSTALLINE CELLULOSE; ISOPROPYL ALCOHOL; AMMONIUM ACRYLOYLDIMETHYLTAURATE/VP COPOLYMER; BUTYROSPERMUM PARKII (SHEA) BUTTER UNSAPONIFIABLES; PHENOXYETHANOL; MODIFIED CORN STARCH (1-OCTENYL SUCCINIC ANHYDRIDE); ARNICA MONTANA; WATER; WITCH HAZEL; HYDRATED SILICA; GLYCERIN; POLYGLYCERYL-10 CAPRYLATE; BIOSACCHARIDE GUM-1

KT Recovery Plus

Active Ingredients Purpose

Camphor (5%) External Analgesic
Menthol (5%) External Analgesic

Uses:
for the temporary relief of minor aches and pains of muscles and joints due to:
* simple backache * arthritis * sprains * strains * bruises

Warnings:
* for external use only * do not apply to wounds or damaged skin or bandage tightly * avoid contact with eyes * Keep out of reach of children. if swallowed, get medical help or contact a Poison Control Center immediately * if condition worsens, or if symptoms persist for more than 7 days, or clear up and occur again within a few days, discontinue use of this product and consult a physician * Pregnancy-breast feeding warning: if pregnant or breast feeding, ask a health professional before use * do not bandage tightly

Inactive Ingredients:
distilled water, hamamelis virginiana (witch hazel extract),
ethanol alcohol, arnica Montana, oleyl alcohol and
zanthoxylum alatum (scezhuan pepper), Bio-saccharide
Gum -1, glycerin, ammonium acryloyldimethyltaurate/VP
copolymer, beta cyclodextrin, menthol, potassium hydroxide,
mannitol, cellulose chromium, hydroxide green, tocopheryl
acetate (vitamin E), hydroxypropyl methycellulose

Directions:
for adults and children 2 years and older; apply to affected area not more than 3 to 4 times daily. "Children under 2 years of age: consult a doctor." Apply generously to affected and surrounding areas. Rub in well. Use 1 application for minor pain, 2 for medium and 3 applications for severs symptoms. Allow to dry between applications (usually just 2-3 minutes).

Directions:
for adults and children 2 years and older; apply to affected area not more than 3 to 4 times daily. "Children under 2 years of age: consult a doctor." Apply generously to affected and surrounding areas. Rub in well. Use 1 application for minor pain, 2 for medium and 3 applications for severs symptoms. Allow to dry between applications (usually just 2-3 minutes).

Uses:
for the temporary relief of minor aches and pains of muscles
and joints due to:
* simple backache
* arthritis
* sprains
* strains
* bruises

Warnings:
* for external use only
* do not apply to wounds or damaged skin or bandage tightly
* avoid contact with eyes
* Keep out of reach of children. if swallowed, get medical help or contact a Poison Control Center immediately
* if condition worsens, or if symptoms persist for more than 7 days, discontinue use of this product and consult a physician
* Pregnancy-breast feeding warning: if pregnant or breast feeding, ask a health professional before use
* do not bandage tightly

PACKAGE LABEL

An image/jpeg of the container label is included in this section.